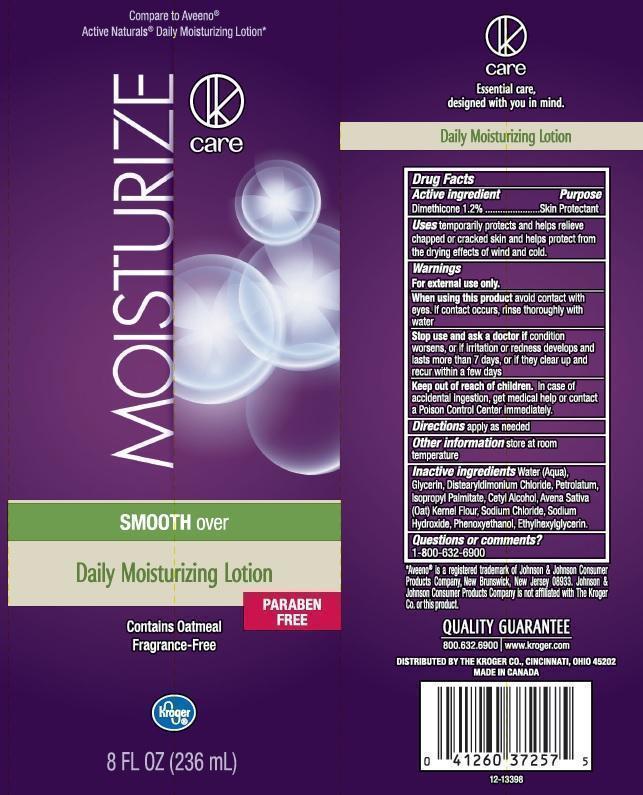 DRUG LABEL: KROGER
NDC: 30142-319 | Form: LIQUID
Manufacturer: THE KROGER COMPANY
Category: otc | Type: HUMAN OTC DRUG LABEL
Date: 20150121

ACTIVE INGREDIENTS: DIMETHICONE 12 mg/1 mL
INACTIVE INGREDIENTS: WATER; GLYCERIN; DISTEARYLDIMONIUM CHLORIDE; PETROLATUM; ISOPROPYL PALMITATE; CETYL ALCOHOL; OATMEAL; SODIUM CHLORIDE; SODIUM HYDROXIDE; PHENOXYETHANOL; ETHYLHEXYLGLYCERIN

DRUG FACTS

ACTIVE INGREDIENT

DIMETHICONE 1.2%

PURPOSE

SKIN PROTECTANT

USES

TEMPORARILY PROTECTS AND HELPS RELIEVE CHAPPED OR CRACKED SKIN AND HELPS PROTECT FROM THE DRYING EFFECTS OF WIND AND COLD

WARNINGS

FOR EXTERNAL USE ONLY

WHEN USING THIS PRODUCT

AVOID CONTACT WITH EYES. IF CONTACT OCCURS, RINSE THOROUGHLY WITH WATER

STOP USE AND ASK A DOCTOR IF

CONDITION WORSENS, OR IF IRRITATION OR REDNESS DEVELOPS AND LASTS MORE THAN 7 DAYS, OR IF THEY CLEAR UP AND RECUR WITHIN A FEW DAYS

KEEP OUT OF REACH OF CHILDREN

IN CASE OF ACCIDENTAL INGESTION, GET MEDICAL HELP OR CONTACT A POISON CONTROL CENTER IMMEDIATELY

DIRECTIONS

APPLY AS NEEDED

OTHER INFORMATION

STORE AT ROOM TEMPERATURE

INACTIVE INGREDIENTS

WATER (AQUA), GLYCERIN, DISTEARYLDIMONIUM CHLORIDE, PETROLATUM, ISOPROPYL PALMITATE, CETYL ALCOHOL, AVENA SATIVA (OAT) KERNEL FLOUR, SODIUM CHLORIDE, SODIUM HYDROXIDE, PHENOXYETHANOL, ETHYLHEXYLGLYCERIN

QUESTIONS OR COMMENTS?

1-800-632-6900